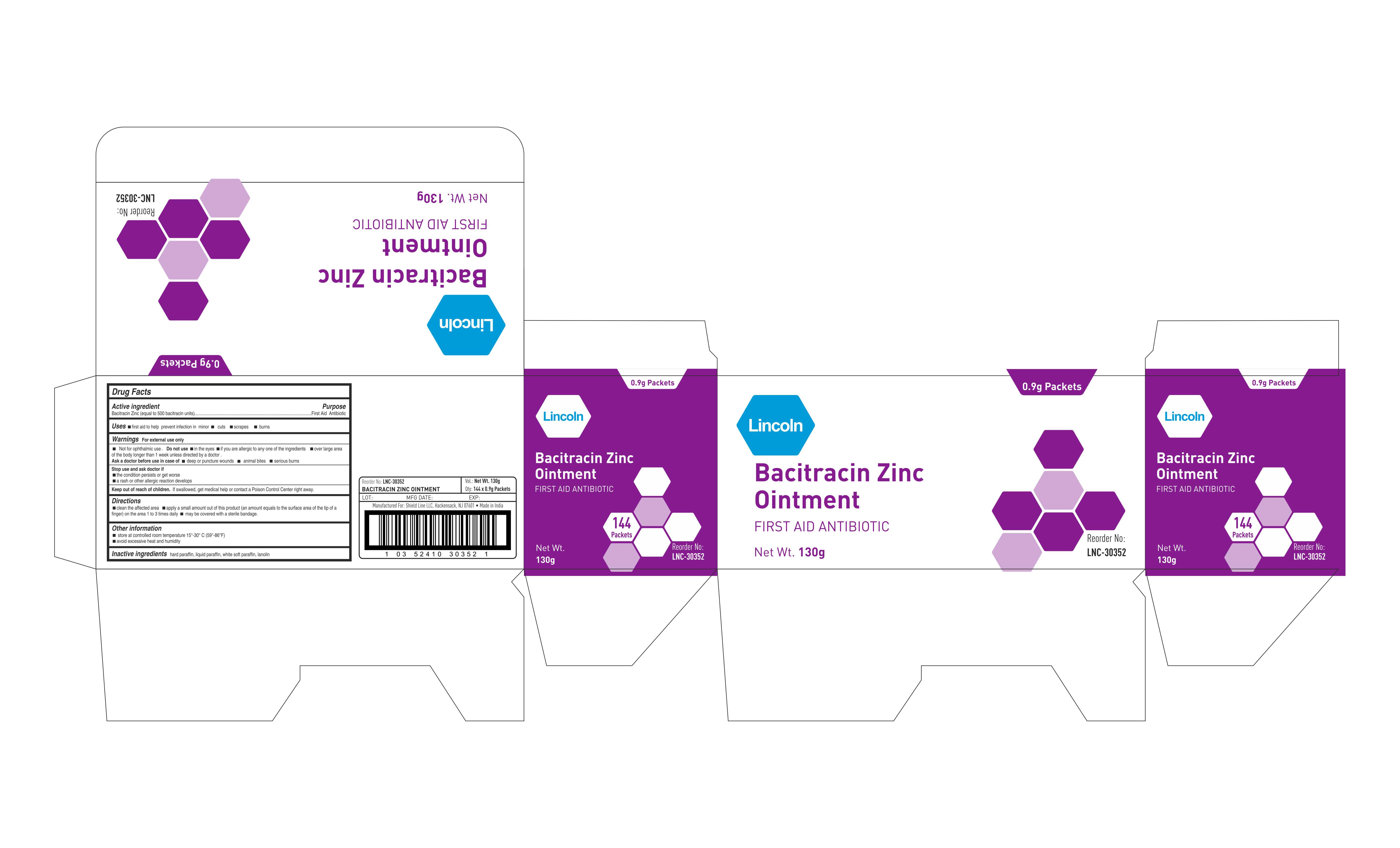 DRUG LABEL: Lincoln
NDC: 69636-3035 | Form: OINTMENT
Manufacturer: Lincoln Pharmaceuticals Ltd.
Category: otc | Type: HUMAN OTC DRUG LABEL
Date: 20160408

ACTIVE INGREDIENTS: BACITRACIN ZINC 500 [USP'U]/1 g
INACTIVE INGREDIENTS: MINERAL OIL; LANOLIN; PETROLATUM; PARAFFIN

Drug Facts

Active Ingredient (in each gram)

Bacitracin Zinc (equal to 500 bacitracin units)

Drug Facts

First Aid Antibiotic

Drug Facts

Uses

- first aid to help prevent infection in minor
- cuts scrapes
- burns

Drug Facts

For External use only

Do not use

- in the eyes
- if you are allergenic to any of the ingredients
- over large area of the body longer than 1 week unless directed by a doctor

Drug Facts

- deep or puncture wounds
- animal bites
- serious burns

Drug Facts

- the condition persists or get worse
- a rash or other allergic reaction develops

Drug Facts

Keep out of reach of children

- if swallowed, get medical help or Contact a Poison Control Center right away

Drug Facts

- clean the affected area
- apply a small amount of this product (an amount equals to the surface area of the tip of a finger) on the area 1 to 3 times daily
- may be covered with a sterile bandage

Drug Facts

Other information:

- store at controlled temperature 15°-30° C
- Avoid excessive heat and humidity

Drug Facts

Inactive ingredients

hard paraffin, liquid paraffin, white soft paraffin, lanolin